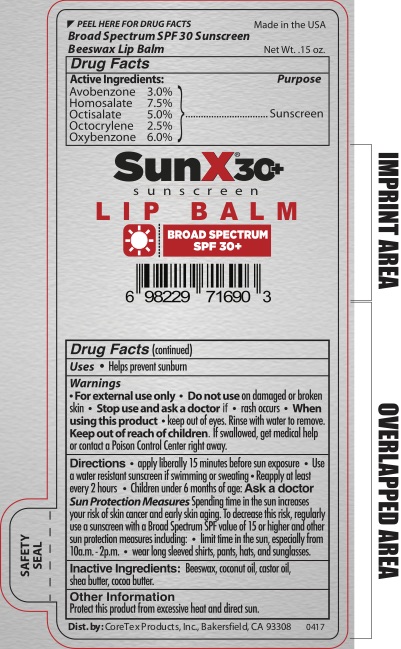 DRUG LABEL: Sun XSPF 30 Broad Spectrum Sunscreen Lip Balm
NDC: 65753-105 | Form: LIPSTICK
Manufacturer: CoreTex Products, INC
Category: otc | Type: HUMAN OTC DRUG LABEL
Date: 20191125

ACTIVE INGREDIENTS: OCTISALATE 5 g/100 mL; OCTOCRYLENE 2.5 g/100 mL; OXYBENZONE 6 g/100 mL; AVOBENZONE 3 g/100 mL; HOMOSALATE 7.5 g/100 mL
INACTIVE INGREDIENTS: COCONUT OIL; WHITE WAX; SHEA BUTTER; COCOA BUTTER

Sun X Lip Balm

Active Ingredients

Avobenzone…3.0%

Homosalate…7.5%

Octisalate…5.0%

Octocrylene…2.5%

Oxybenzone…6.0%

Purpose

Sunscreen

Uses

Helps prevent sunburn.

WARNINGS

- For external use only

Do not use on damaged or broken skin.

Stop use and ask a doctor if

- rash occurs

When using this product

- keep out of eyes. Rinse to remove.

Keep out of reach of children. If swallowed, get medical help or contact a Poison Control Center right away.

Directions

- apply liberally 15 minutes before sun exposure
- Use water resistant sunscreen if swimming or sweating
- Reapply at least every 2 hours
- Children under 6 months of age: Ask a doctor

Sun Protection Measures

Spending time in the sun increases your risk of skin cancer and early skin aging. To decrease this risk, regularly use a sunscreen with a Broad Spectrum SPF value of 15 or higher and other sun protection measures:

- limit time in the sun, especially from 10a.m.-2p.m.
- wear long sleeved shirts, pants, hats, and sunglasses.

Inactive Ingredients

Beeswax, castor oil, cocoa butter, coconut oil, shea utter

Other Information

Protect this productfrom excessive heat and direct sun.